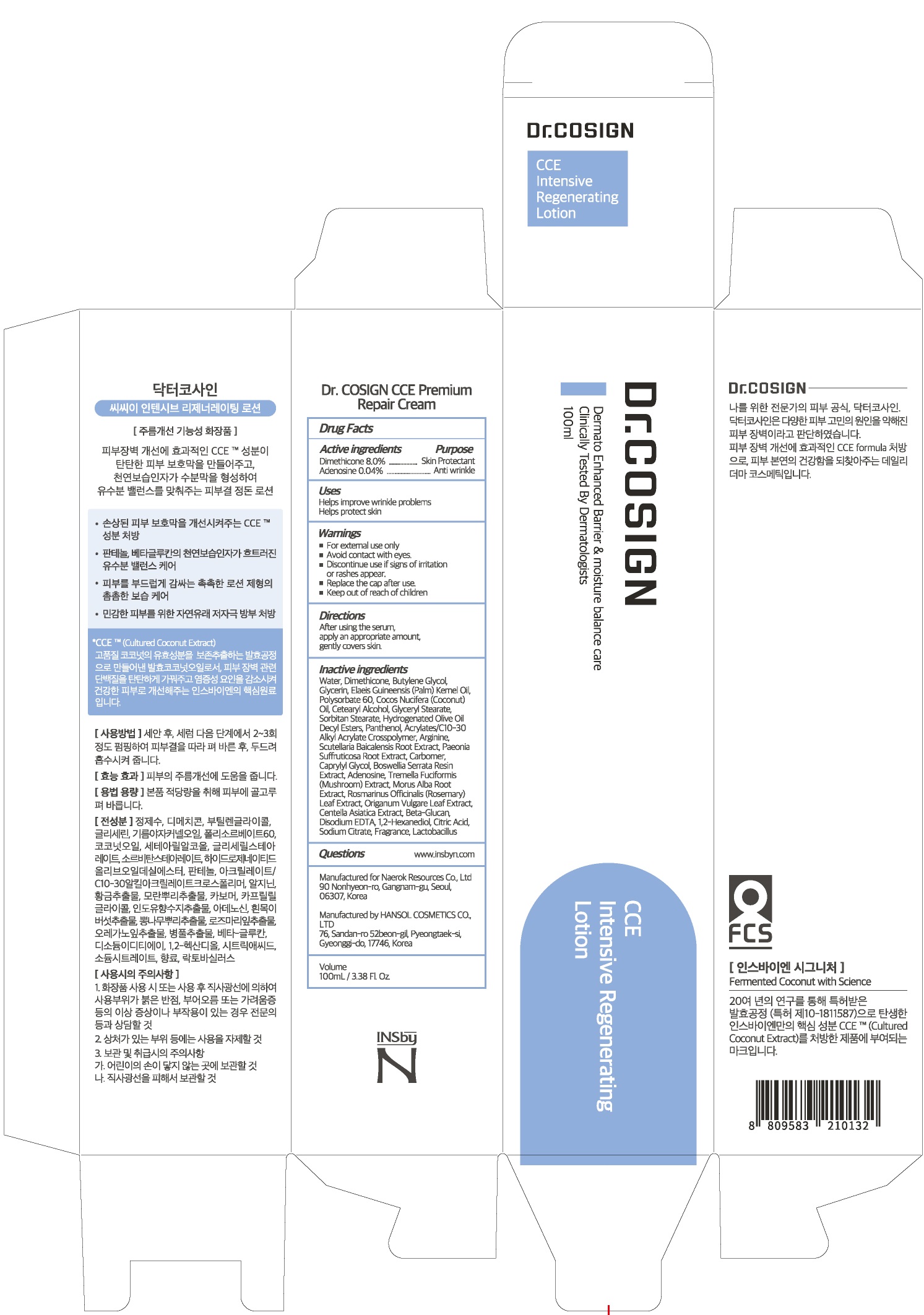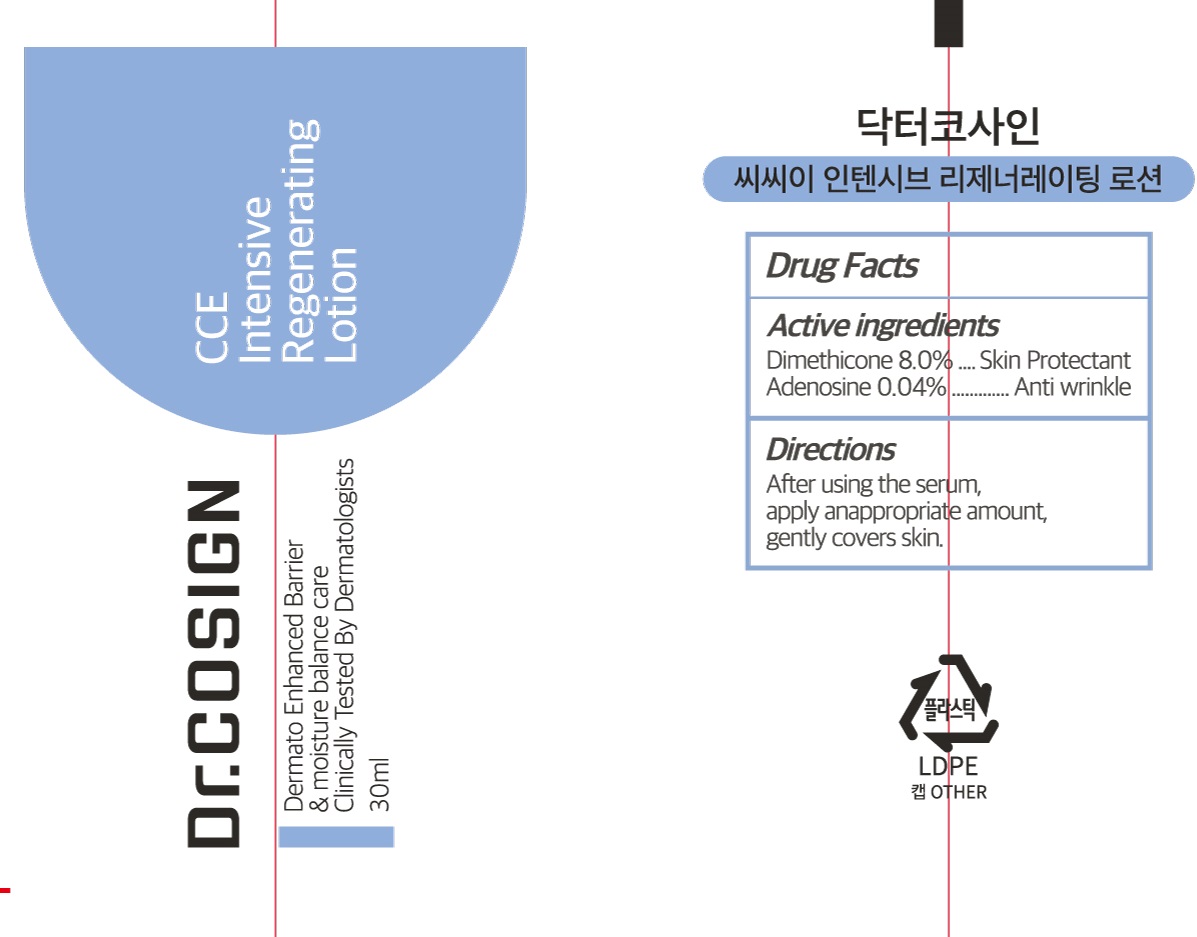 DRUG LABEL: Dr COSIGN CCE Intensive Regenerating
NDC: 72642-010 | Form: LOTION
Manufacturer: Naerok Resources Co., Ltd
Category: otc | Type: HUMAN OTC DRUG LABEL
Date: 20181106

ACTIVE INGREDIENTS: Dimethicone 8.0 g/100 mL; Adenosine 0.04 g/100 mL
INACTIVE INGREDIENTS: Water; Butylene Glycol

ACTIVE INGREDIENT

Active ingredients: Dimethicone 8.0%, Adenosine 0.04%

INACTIVE INGREDIENT

Inactive ingredients:

Water, Butylene Glycol, Glycerin, Elaeis Guineensis (Palm) Kernel Oil, Polysorbate 60, Cocos Nucifera (Coconut) Oil, Cetearyl Alcohol, Glyceryl Stearate, Sorbitan Stearate, Hydrogenated Olive Oil Decyl Esters, Panthenol, Acrylates/C10-30 Alkyl Acrylate Crosspolymer, Arginine, Scutellaria Baicalensis Root Extract, Paeonia Suffruticosa Root Extract, Carbomer, Caprylyl Glycol, Boswellia Serrata Resin Extract, Tremella Fuciformis (Mushroom) Extract, Morus Alba Root Extract, Rosmarinus Officinalis (Rosemary) Leaf Extract, Origanum Vulgare Leaf Extract, Centella Asiatica Extract, Beta-Glucan, Disodium EDTA, 1,2-Hexanediol, Citric Acid, Sodium Citrate, Fragrance, Lactobacillus

PURPOSE

Purpose: Skin Protectant, Anti wrinkle

WARNINGS

For external use only

Avoid contact with eyes.

Discontinue use if signs of irritation or rashes appear.

Replace the cap after use.

Keep out of reach of children

KEEP OUT OF REACH OF CHILDREN

Uses

Helps improve wrinkle problems

Helps protect skin

Directions

After using the serum, apply an appropriate amount, gently covers skin.